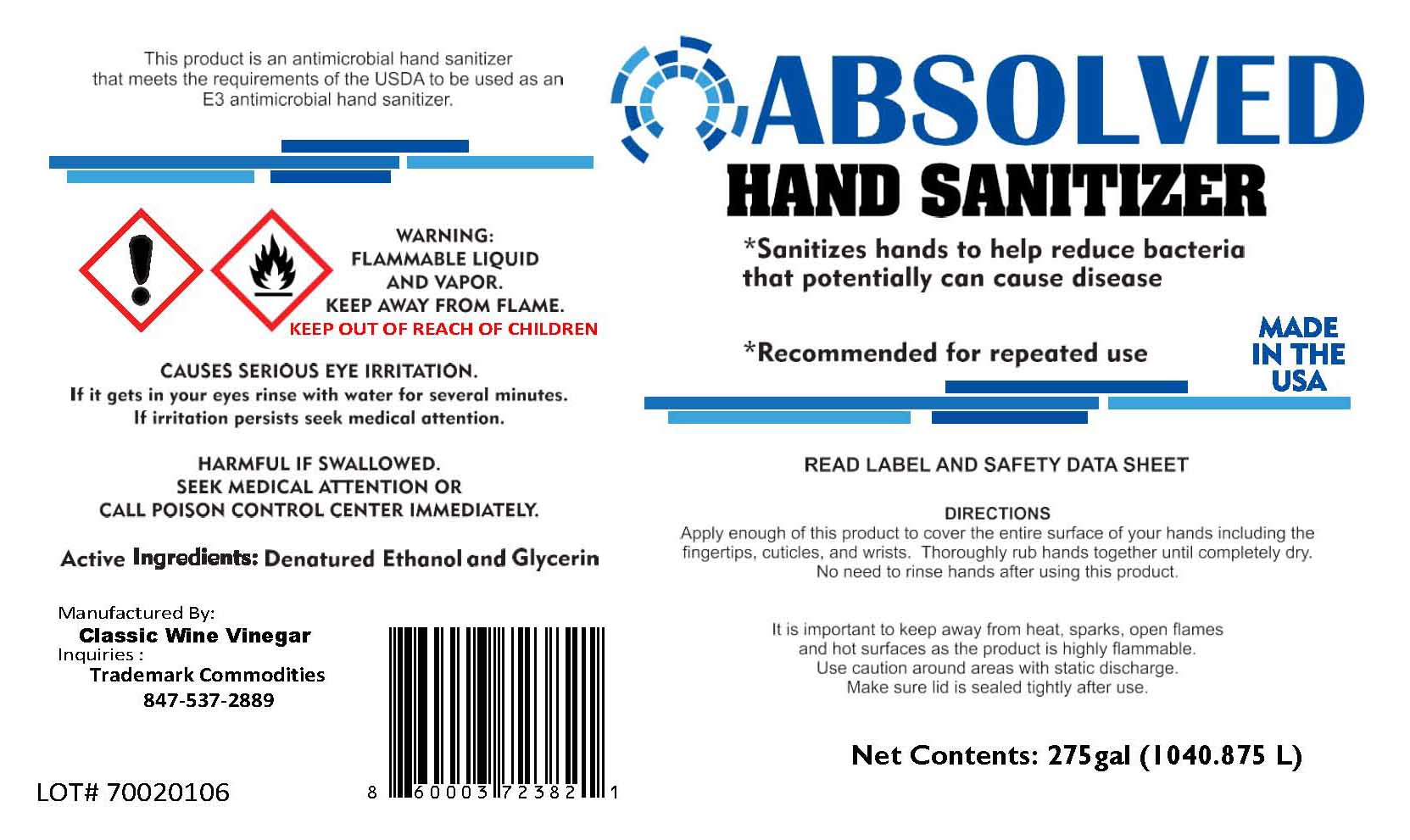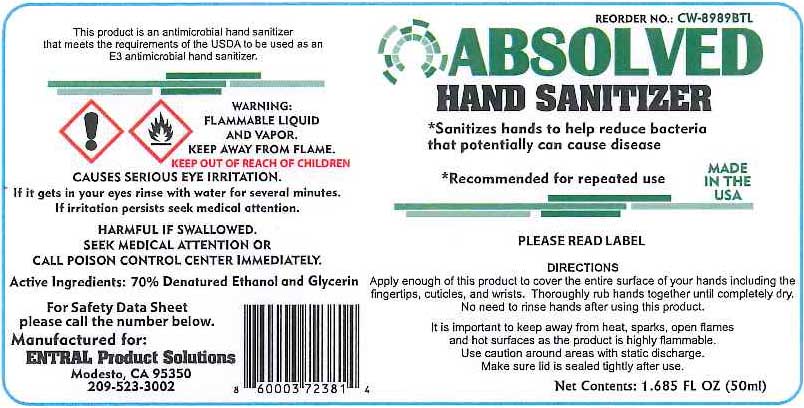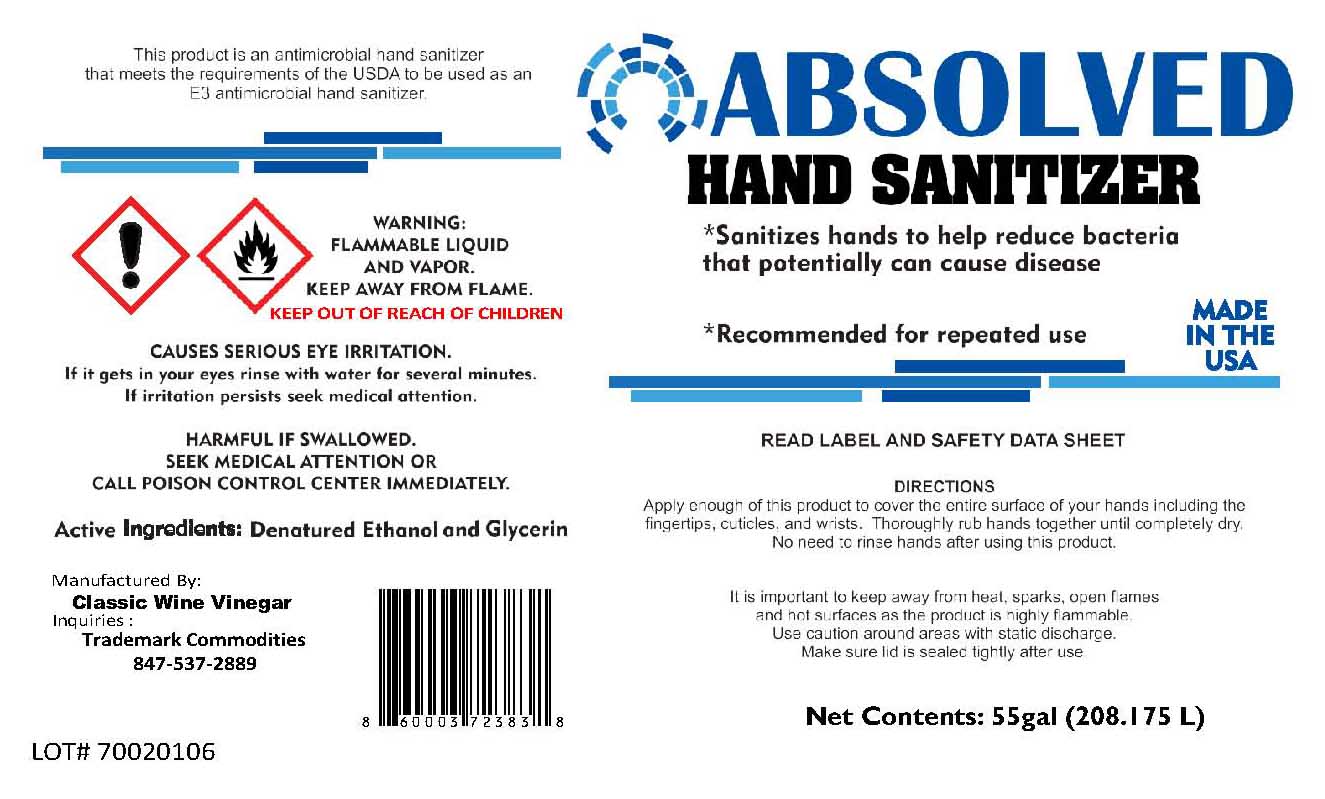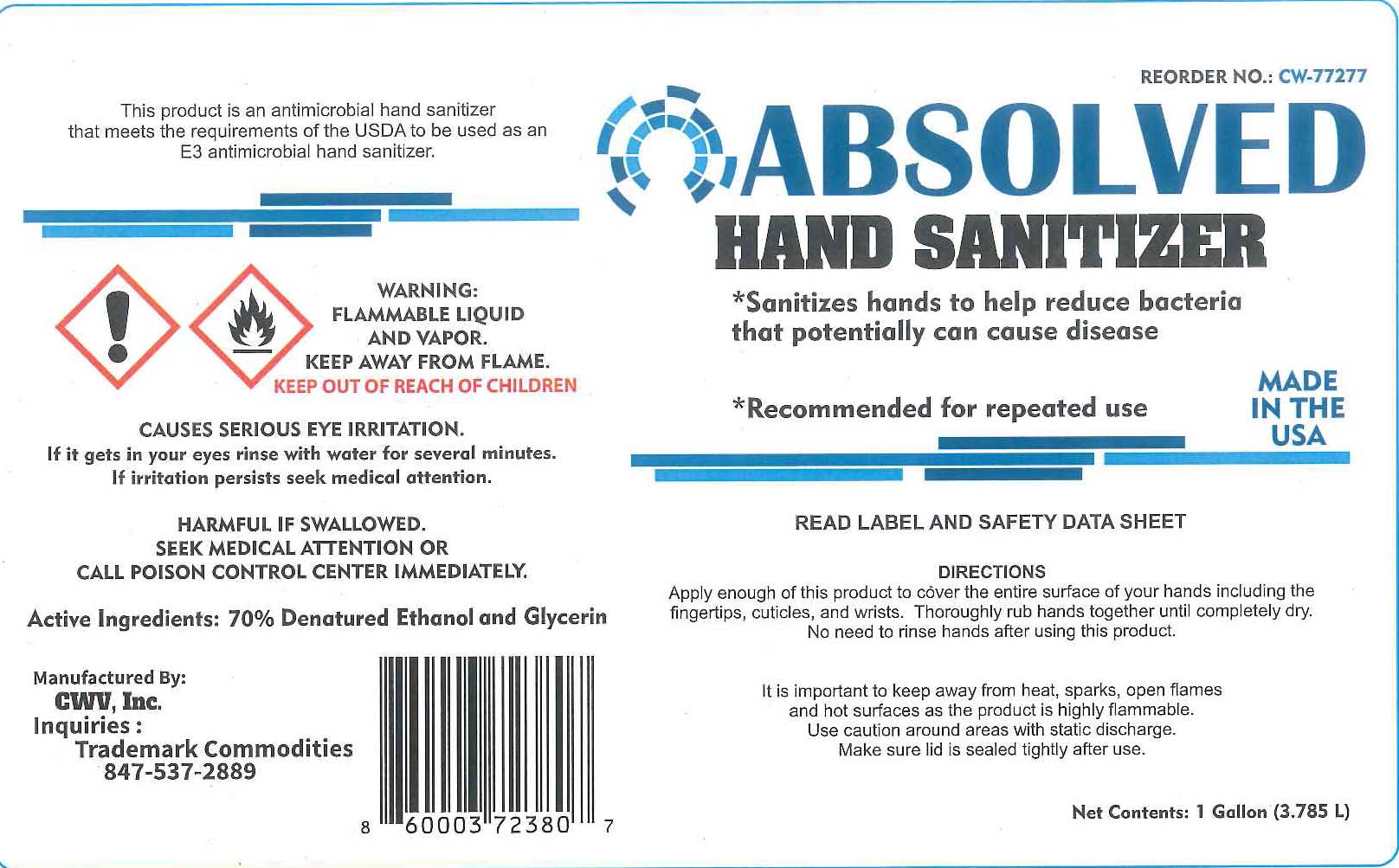 DRUG LABEL: Hand Sanitizer
NDC: 75600-807 | Form: LIQUID
Manufacturer: CLASSIC WINE VINEGAR COMPANY INC
Category: otc | Type: HUMAN OTC DRUG LABEL
Date: 20200420

ACTIVE INGREDIENTS: ALCOHOL 80 mL/100 mL
INACTIVE INGREDIENTS: GLYCERIN 1.45 mL/100 mL; WATER

This is a hand sanitizer manufactured according to the Temporary Policy for Preparation of Certain Alcohol-Based Hand Sanitizer Products During the Public Health Emergency (CoViD-19); Guidance for Industry.

The hand sanitizer is manufactured using only the following United States Pharmacopoeia (USP) grade ingredients in the preparation of the product (percentage in final product formulation) consistent with World Health Organization (WHO) recommendations:

1. Alcohol (ethanol) (USP or Food Chemical Codex (FCC) grade) (80%, volume/volume (v/v)) in an aqueous solution denatured according to Alcohol and Tobacco Tax and Trade Bureau regulations in 27 CFR part 20.
2. Glycerol (1.45% v/v).
3. Purified cold water.

The firm does not add other active or inactive ingredients. Different or additional ingredients may impact the quality and potency of the product.

Active Ingredient(s)

DENATURED ETHANOL AND GLYCERIN

Purpose

THIS PRODUCT IS AN ANTIMICROBIAL HAND SANITIZER THAT MEETS THE REQUIREMENTS OF THE USDA TO BE USED AS AN E3 ANTIMICROBIAL HAND SANITIZER.

SANITIZES HANDS TO HELP REDUCE BACTERIA THAT POTENTIALLY CAN CAUSE DISEASE

Use

Hand Sanitizer to help reduce bacteria that potentially can cause disease. For use when soap and water are not available.

Warnings

FLAMMABLE LIQUID AND VAPOR. KEEP AWAY FROM FLAME.

CAUSES SERIOUS EYE IRRITATION. IF IT GETS IN YOUR EYES RINSE WITH WATER FOR SEVERAL MINUTES. IF IRRITATION PERSISTS SEEK MEDICAL ATTENTION.

HARMFUL IF SWALLED SEEK MEDICAL ATTENTION OR CALL POISON CONTROL CENTER IMMEDIATELY.

IT IS MPORTANT TO KEEP AWAY FROM HEAT, SPARKS, OPEN FLAMES AND HOT SURFACES AS THIS PRODUCT IS HIGHLY FLAMMABLE. USE CAUTION AROUND AREAS WITH STATIC DISCHARGE. AKE SURE LID IS SEALED TIGHTLY AFTER USE.

WHEN USING

CAUSES SERIOUS EYE IRRITATION. IF IT GETS IN YOUR EYES RINSE WITH WATER FOR SEVERAL MINUTES. IF IRRITATION PERSISTS SEEK MEDICAL ATTENTION. HARMFUL IF SWALLOWED. SEEK MEDICAL ATTENTION OR CALL POISON CONTROL CENTER IMMEDIATELY

Directions

APPLY ENOUGH OF THIS PRODUCT TO COVER THE ENTIRE SURFACE OF YOUR HANDS INCLUDING THE FINGERTIPS, CUTICLES, AND WRISTS. THOROUGHY RUB HANDS TOGETHER UNTIL COMPLETELY DRY. NO NEED TO RINSE HANDS AFTER USING THIS PRODUCT..

Inactive ingredients

glycerin, purified water USP

KEEP OUT OF REACH OF CHILDREN

Package Label - Principal Display Panel

50mL NDC: 75600-807-50

3785mL NDC: 75600-807-01

208197mL NDC: 75600-807-55

1040988 mL NDC: 75600-807-27